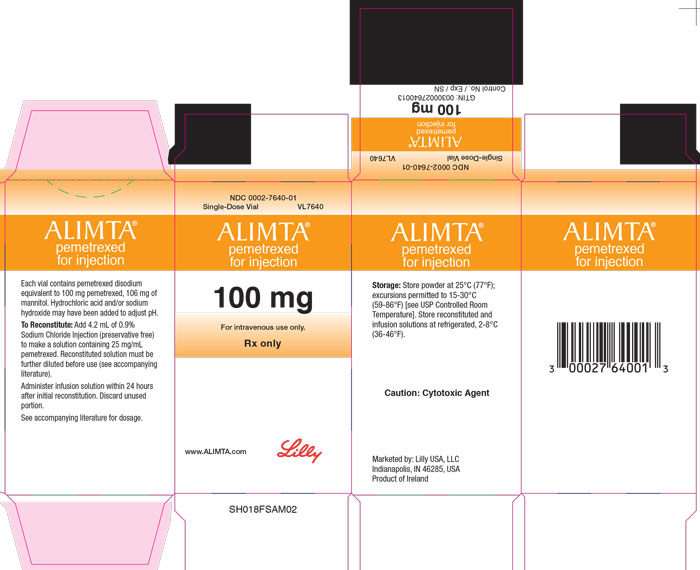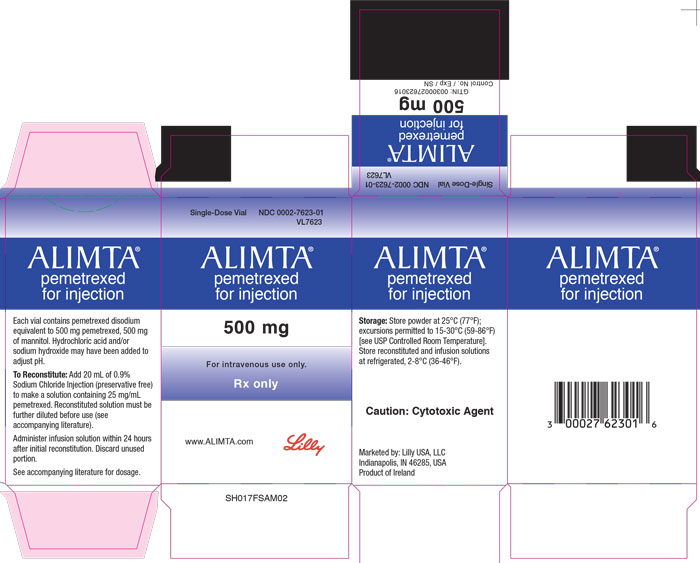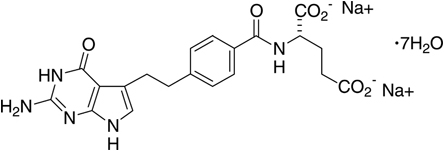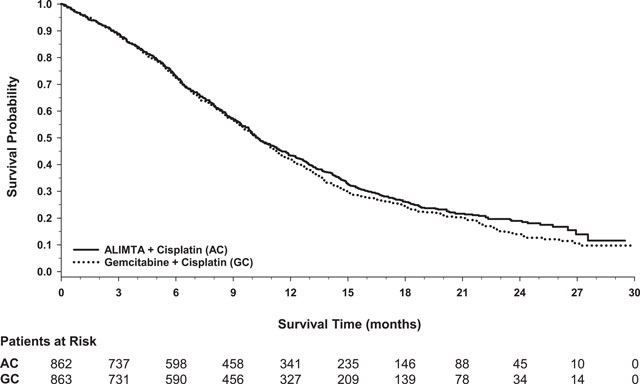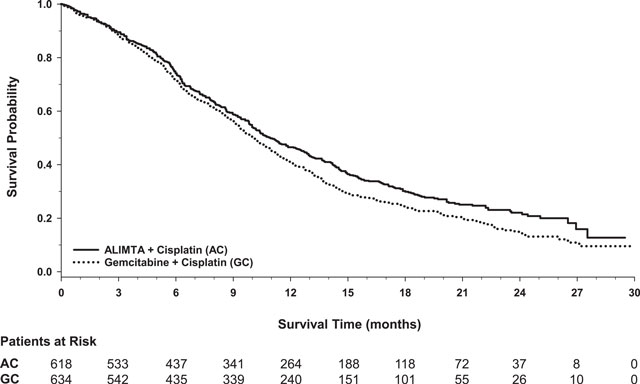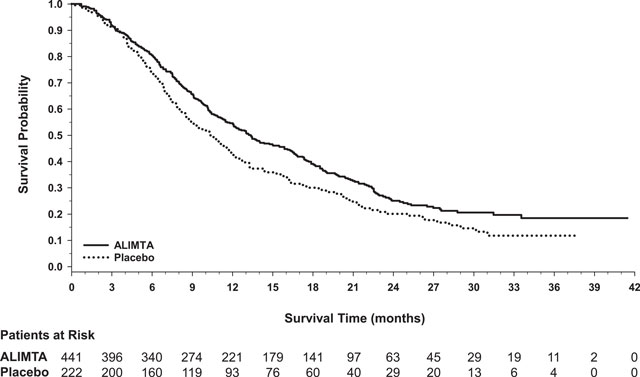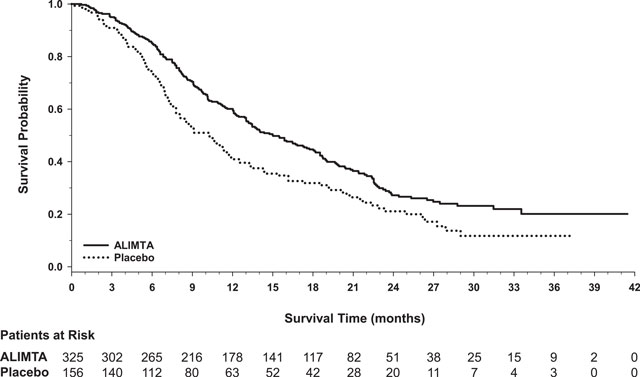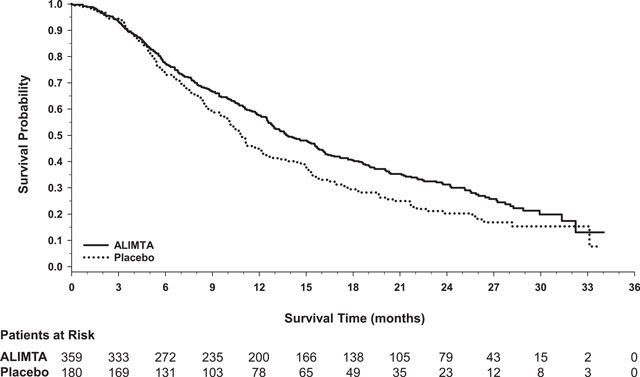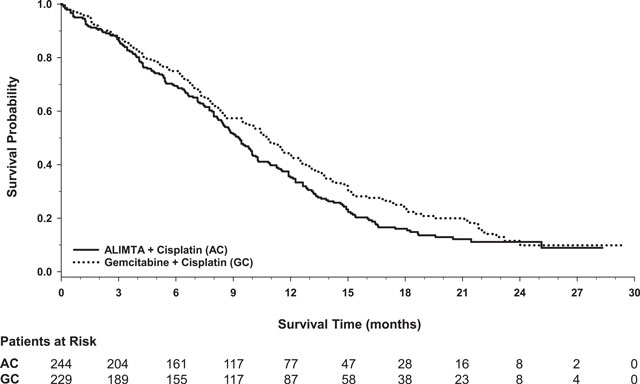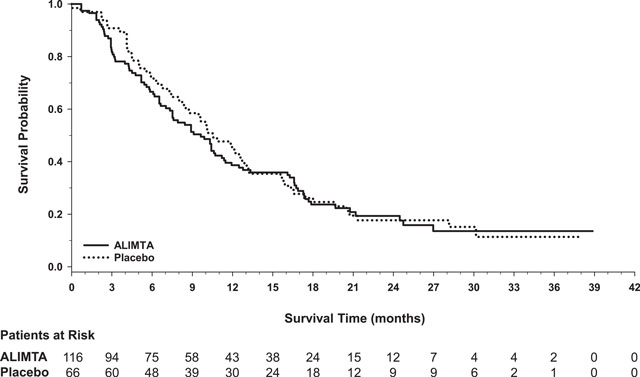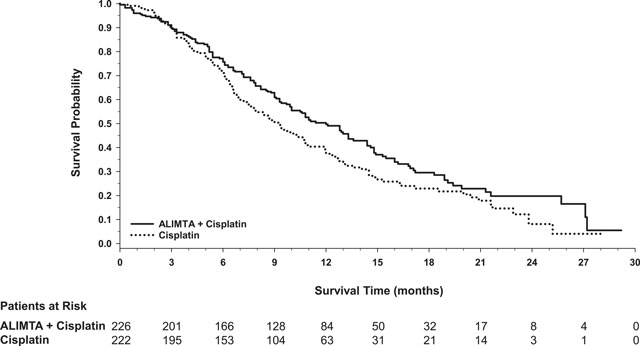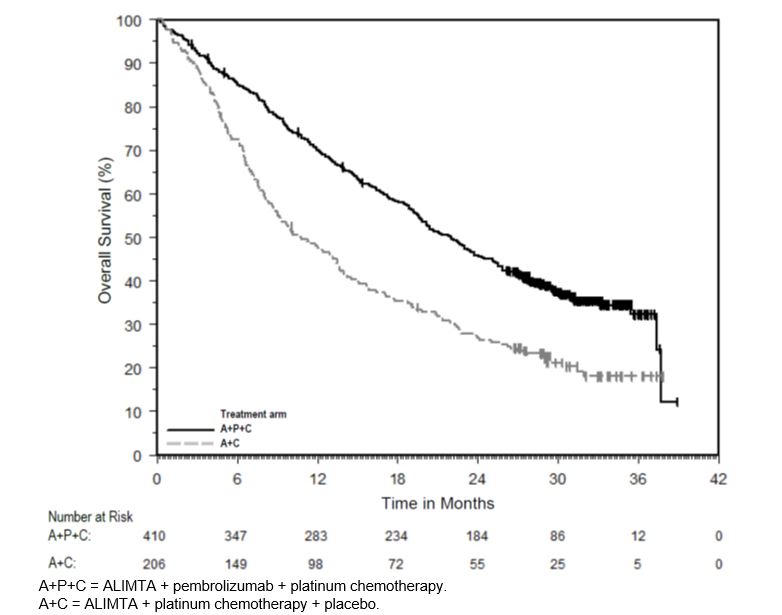 DRUG LABEL: Alimta
NDC: 0002-7640 | Form: INJECTION, POWDER, LYOPHILIZED, FOR SOLUTION
Manufacturer: Eli Lilly and Company
Category: prescription | Type: HUMAN PRESCRIPTION DRUG LABEL
Date: 20230519

ACTIVE INGREDIENTS: Pemetrexed disodium heptahydrate 100 mg/4 mL
INACTIVE INGREDIENTS: Mannitol 106 mg/4 mL; Hydrochloric acid; Sodium hydroxide

HIGHLIGHTS OF PRESCRIBING INFORMATION

These highlights do not include all the information needed to use ALIMTA safely and effectively. See full prescribing information for ALIMTA.
ALIMTA (pemetrexed for injection), for Intravenous Use
Initial U.S. Approval: 2004

1 INDICATIONS AND USAGE

ALIMTA® is a folate analog metabolic inhibitor indicated:

- in combination with pembrolizumab and platinum chemotherapy, for the initial treatment of patients with metastatic non-squamous non-small cell lung cancer (NSCLC), with no EGFR or ALK genomic tumor aberrations. (1.1)
- in combination with cisplatin for the initial treatment of patients with locally advanced or metastatic, non-squamous NSCLC. (1.1)
- as a single agent for the maintenance treatment of patients with locally advanced or metastatic, non-squamous NSCLC whose disease has not progressed after four cycles of platinum-based first-line chemotherapy. (1.1)
- as a single agent for the treatment of patients with recurrent, metastatic non-squamous, NSCLC after prior chemotherapy. (1.1)
  Limitations of Use: ALIMTA is not indicated for the treatment of patients with squamous cell, non-small cell lung cancer. (1.1)
- initial treatment, in combination with cisplatin, of patients with malignant pleural mesothelioma whose disease is unresectable or who are otherwise not candidates for curative surgery. (1.2)

2 DOSAGE AND ADMINISTRATION

- The recommended dose of ALIMTA administered with pembrolizumab and platinum chemotherapy in patients with a creatinine clearance (calculated by Cockcroft-Gault equation) of 45 mL/min or greater is 500 mg/m^2 as an intravenous infusion over 10 minutes, administered after pembrolizumab and prior to platinum chemotherapy, on Day 1 of each 21-day cycle. (2.1)
- The recommended dose of ALIMTA, administered as a single agent or with cisplatin, in patients with creatinine clearance of 45 mL/minute or greater is 500 mg/m^2 as an intravenous infusion over 10 minutes on Day 1 of each 21-day cycle. (2.1, 2.2)
- Initiate folic acid 400 mcg to 1000 mcg orally, once daily, beginning 7 days prior to the first dose of ALIMTA and continue until 21 days after the last dose of ALIMTA. (2.4)
- Administer vitamin B12, 1 mg intramuscularly, 1 week prior to the first dose of ALIMTA and every 3 cycles. (2.4)
- Administer dexamethasone 4 mg orally, twice daily the day before, the day of, and the day after ALIMTA administration. (2.4)

3 DOSAGE FORMS AND STRENGTHS

For Injection: 100 mg or 500 mg lyophilized powder in single-dose vial (3)

4 CONTRAINDICATIONS

History of severe hypersensitivity reaction to pemetrexed. (4)

5 WARNINGS AND PRECAUTIONS

- Myelosuppression: Can cause severe bone marrow suppression resulting in cytopenia and an increased risk of infection. Do not administer ALIMTA when the absolute neutrophil count is less than 1500 cells/mm^3 and platelets are less than 100,000 cells/mm^3. Initiate supplementation with oral folic acid and intramuscular vitamin B12 to reduce the severity of hematologic and gastrointestinal toxicity of ALIMTA. (2.4, 5.1)
- Renal Failure: Can cause severe, and sometimes fatal, renal failure. Do not administer when creatinine clearance is less than 45 mL/min. (2.3, 5.2)
- Bullous and Exfoliative Skin Toxicity: Permanently discontinue for severe and life-threatening bullous, blistering or exfoliating skin toxicity. (5.3)
- Interstitial Pneumonitis: Withhold for acute onset of new or progressive unexplained pulmonary symptoms. Permanently discontinue if pneumonitis is confirmed. (5.4)
- Radiation Recall: Can occur in patients who received radiation weeks to years previously; permanently discontinue for signs of radiation recall. (5.5)
- Embryo-Fetal Toxicity: Can cause fetal harm. Advise patients of the potential risk to a fetus and to use effective contraception. (5.7, 8.1, 8.3)

6 ADVERSE REACTIONS

- The most common adverse reactions (incidence ≥20%) of ALIMTA, when administered as a single agent are fatigue, nausea, and anorexia. (6.1)
- The most common adverse reactions (incidence ≥20%) of ALIMTA when administered with cisplatin are vomiting, neutropenia, anemia, stomatitis/pharyngitis, thrombocytopenia, and constipation. (6.1)
- The most common adverse reactions (incidence ≥20%) of ALIMTA when administered in combination with pembrolizumab and platinum chemotherapy are fatigue/asthenia, nausea, constipation, diarrhea, decreased appetite, rash, vomiting, cough, dyspnea, and pyrexia. (6.1)

To report SUSPECTED ADVERSE REACTIONS, contact Eli Lilly and Company at 1-800-LillyRx (1-800-545-5979) or FDA at 1-800-FDA-1088 or www.fda.gov/medwatch.

7 DRUG INTERACTIONS

Ibuprofen increased risk of ALIMTA toxicity in patients with mild to moderate renal impairment. Modify the ibuprofen dosage as recommended for patients with a creatinine clearance between 45 mL/min and 79 mL/min. (2.5, 5.6, 7)

8 USE IN SPECIFIC POPULATIONS

Lactation: Advise not to breastfeed. (8.2)

FULL PRESCRIBING INFORMATION

1 INDICATIONS AND USAGE

1.1 Non-Squamous Non-Small Cell Lung Cancer (NSCLC)

ALIMTA® is indicated:

- in combination with pembrolizumab and platinum chemotherapy, for the initial treatment of patients with metastatic non-squamous non-small cell lung cancer (NSCLC), with no EGFR or ALK genomic tumor aberrations.
- in combination with cisplatin for the initial treatment of patients with locally advanced or metastatic, non-squamous NSCLC.
- as a single agent for the maintenance treatment of patients with locally advanced or metastatic, non-squamous NSCLC whose disease has not progressed after four cycles of platinum-based first-line chemotherapy.
- as a single agent for the treatment of patients with recurrent, metastatic non-squamous, NSCLC after prior chemotherapy.

Limitations of Use: ALIMTA is not indicated for the treatment of patients with squamous cell, non-small cell lung cancer [see Clinical Studies (14.1)].

1.2 Mesothelioma

ALIMTA is indicated, in combination with cisplatin, for the initial treatment of patients with malignant pleural mesothelioma whose disease is unresectable or who are otherwise not candidates for curative surgery.

2 DOSAGE AND ADMINISTRATION

2.1 Recommended Dosage for Non-Squamous NSCLC

- The recommended dose of ALIMTA when administered with pembrolizumab and platinum chemotherapy for the initial treatment of metastatic non-squamous NSCLC in patients with a creatinine clearance (calculated by Cockcroft-Gault equation) of 45 mL/min or greater is 500 mg/m^2 as an intravenous infusion over 10 minutes administered after pembrolizumab and prior to carboplatin or cisplatin on Day 1 of each 21-day cycle for 4 cycles. Following completion of platinum-based therapy, treatment with ALIMTA with or without pembrolizumab is administered until disease progression or unacceptable toxicity. Please refer to the full prescribing information for pembrolizumab and for carboplatin or cisplatin.
- The recommended dose of ALIMTA when administered with cisplatin for initial treatment of locally advanced or metastatic non-squamous NSCLC in patients with a creatinine clearance (calculated by Cockcroft-Gault equation) of 45 mL/min or greater is 500 mg/m^2 as an intravenous infusion over 10 minutes administered prior to cisplatin on Day 1 of each 21-day cycle for up to six cycles in the absence of disease progression or unacceptable toxicity.
- The recommended dose of ALIMTA for maintenance treatment of non-squamous NSCLC in patients with a creatinine clearance (calculated by Cockcroft-Gault equation) of 45 mL/min or greater is 500 mg/m^2 as an intravenous infusion over 10 minutes on Day 1 of each 21-day cycle until disease progression or unacceptable toxicity after four cycles of platinum-based first-line chemotherapy.
- The recommended dose of ALIMTA for treatment of recurrent non-squamous NSCLC in patients with a creatinine clearance (calculated by Cockcroft-Gault equation) of 45 mL/min or greater is 500 mg/m^2 as an intravenous infusion over 10 minutes on Day 1 of each 21-day cycle until disease progression or unacceptable toxicity.

2.2 Recommended Dosage for Mesothelioma

- The recommended dose of ALIMTA when administered with cisplatin in patients with a creatinine clearance (calculated by Cockcroft-Gault equation) of 45 mL/min or greater is 500 mg/m^2 as an intravenous infusion over 10 minutes on Day 1 of each 21-day cycle until disease progression or unacceptable toxicity.

2.3 Renal Impairment

- ALIMTA dosing recommendations are provided for patients with a creatinine clearance (calculated by Cockcroft-Gault equation) of 45 mL/min or greater [see Dosage and Administration (2.1, 2.2)]. There is no recommended dose for patients whose creatinine clearance is less than 45 mL/min [see Use in Specific Populations (8.6)].

2.4 Premedication and Concomitant Medications to Mitigate Toxicity

Vitamin Supplementation

- Initiate folic acid 400 mcg to 1000 mcg orally once daily, beginning 7 days before the first dose of ALIMTA and continuing until 21 days after the last dose of ALIMTA [see Warnings and Precautions (5.1)].
- Administer vitamin B12, 1 mg intramuscularly, 1 week prior to the first dose of ALIMTA and every 3 cycles thereafter. Subsequent vitamin B12 injections may be given the same day as treatment with ALIMTA [see Warnings and Precautions (5.1)]. Do not substitute oral vitamin B 12 for intramuscular vitamin B 12.

Corticosteroids

- Administer dexamethasone 4 mg orally twice daily for three consecutive days, beginning the day before each ALIMTA administration.

2.5 Dosage Modification of Ibuprofen in Patients with Mild to Moderate Renal Impairment Receiving ALIMTA

In patients with creatinine clearances between 45 mL/min and 79 mL/min, modify administration of ibuprofen as follows [see Warnings and Precautions (5.6), Drug Interactions (7) and Clinical Pharmacology (12.3)]:

- Avoid administration of ibuprofen for 2 days before, the day of, and 2 days following administration of ALIMTA.
- Monitor patients more frequently for myelosuppression, renal, and gastrointestinal toxicity, if concomitant administration of ibuprofen cannot be avoided.

2.6 Dosage Modifications for Adverse Reactions

Obtain complete blood count on Days 1, 8, and 15 of each cycle. Assess creatinine clearance prior to each cycle. Do not administer ALIMTA if the creatinine clearance is less than 45 mL/min.

Delay initiation of the next cycle of ALIMTA until:

- recovery of non-hematologic toxicity to Grade 0-2,
- absolute neutrophil count (ANC) is 1500 cells/mm^3 or higher, and
- platelet count is 100,000 cells/mm^3 or higher.

Upon recovery, modify the dosage of ALIMTA in the next cycle as specified in Table 1.

For dosing modifications for cisplatin, carboplatin, or pembrolizumab, refer to their prescribing information.

Table 1: Recommended Dosage Modifications for Adverse Reactionsa
Toxicity in Most Recent Treatment Cycle | ALIMTA Dose Modification for Next Cycle
Myelosuppressive toxicity [see Warnings and Precautions (5.1)]
ANC less than 500/mm^3 and platelets greater than or equal to 50,000/mm^3 OR Platelet count less than 50,000/mm^3 without bleeding. | 75% of previous dose
Platelet count less than 50,000/mm^3 with bleeding | 50% of previous dose
Recurrent Grade 3 or 4 myelosuppression after 2 dose reductions | Discontinue
Non-hematologic toxicity
Any Grade 3 or 4 toxicities EXCEPT mucositis or neurologic toxicity OR Diarrhea requiring hospitalization | 75% of previous dose
Grade 3 or 4 mucositis | 50% of previous dose
Renal toxicity [see Warnings and Precautions (5.2)] | Withhold until creatinine clearance is 45 mL/min or greater
Grade 3 or 4 neurologic toxicity | Permanently discontinue
Recurrent Grade 3 or 4 non-hematologic toxicity after 2 dose reductions | Permanently discontinue
Severe and life-threatening Skin Toxicity [see Warnings and Precautions (5.3)] | Permanently discontinue
Interstitial Pneumonitis [see Warnings and Precautions (5.4)] | Permanently discontinue
a National Cancer Institute Common Toxicity Criteria for Adverse Events version 2 (NCI CTCAE v2).

2.7 Preparation for Administration

- ALIMTA is a hazardous drug. Follow applicable special handling and disposal procedures.^1
- Calculate the dose of ALIMTA and determine the number of vials needed.
- Reconstitute ALIMTA to achieve a concentration of 25 mg/mL as follows:
  - Reconstitute each 100-mg vial with 4.2 mL of 0.9% Sodium Chloride Injection, USP (preservative-free)
  - Reconstitute each 500-mg vial with 20 mL of 0.9% Sodium Chloride Injection, USP (preservative-free)
  - Do not use calcium-containing solutions for reconstitution.
- Gently swirl each vial until the powder is completely dissolved. The resulting solution is clear and ranges in color from colorless to yellow or green-yellow. FURTHER DILUTION IS REQUIRED prior to administration.
- Store reconstituted, preservative-free product under refrigerated conditions [2-8°C (36-46°F)] for no longer than 24 hours from the time of reconstitution. Discard vial after 24 hours.
- Inspect reconstituted product visually for particulate matter and discoloration prior to further dilution. If particulate matter is observed, discard vial.
- Withdraw the calculated dose of ALIMTA from the vial(s) and discard vial with any unused portion.
- Further dilute ALIMTA with 0.9% Sodium Chloride Injection (preservative-free) to achieve a total volume of 100 mL for intravenous infusion.
- Store diluted, reconstituted product under refrigerated conditions [2-8°C (36-46°F)] for no more than 24 hours from the time of reconstitution. Discard after 24 hours.

3 DOSAGE FORMS AND STRENGTHS

For injection: 100 mg or 500 mg pemetrexed as a white to light-yellow or green-yellow lyophilized powder in single-dose vials for reconstitution.

4 CONTRAINDICATIONS

ALIMTA is contraindicated in patients with a history of severe hypersensitivity reaction to pemetrexed [see Adverse Reactions (6.1)].

5 WARNINGS AND PRECAUTIONS

5.1 Myelosuppression and Increased Risk of Myelosuppression without Vitamin Supplementation

ALIMTA can cause severe myelosuppression resulting in a requirement for transfusions and which may lead to neutropenic infection. The risk of myelosuppression is increased in patients who do not receive vitamin supplementation. In Study JMCH, incidences of Grade 3-4 neutropenia (38% versus 23%), thrombocytopenia (9% versus 5%), febrile neutropenia (9% versus 0.6%), and neutropenic infection (6% versus 0) were higher in patients who received ALIMTA plus cisplatin without vitamin supplementation as compared to patients who were fully supplemented with folic acid and vitamin B12 prior to and throughout ALIMTA plus cisplatin treatment.

Initiate supplementation with oral folic acid and intramuscular vitamin B12 prior to the first dose of ALIMTA; continue vitamin supplementation during treatment and for 21 days after the last dose of ALIMTA to reduce the severity of hematologic and gastrointestinal toxicity of ALIMTA [see Dosage and Administration (2.4)]. Obtain a complete blood count at the beginning of each cycle. Do not administer ALIMTA until the ANC is at least 1500 cells/mm^3 and platelet count is at least 100,000 cells/mm^3. Permanently reduce ALIMTA in patients with an ANC of less than 500 cells/mm^3 or platelet count of less than 50,000 cells/mm^3 in previous cycles [see Dosage and Administration (2.6)].

In Studies JMDB and JMCH, among patients who received vitamin supplementation, incidence of Grade 3-4 neutropenia was 15% and 23%, the incidence of Grade 3-4 anemia was 6% and 4%, and incidence of Grade 3-4 thrombocytopenia was 4% and 5%, respectively. In Study JMCH, 18% of patients in the ALIMTA arm required red blood cell transfusions compared to 7% of patients in the cisplatin arm [see Adverse Reactions (6.1)]. In Studies JMEN, PARAMOUNT, and JMEI, where all patients received vitamin supplementation, incidence of Grade 3-4 neutropenia ranged from 3% to 5%, and incidence of Grade 3-4 anemia ranged from 3% to 5%.

5.2 Renal Failure

ALIMTA can cause severe, and sometimes fatal, renal toxicity. The incidences of renal failure in clinical studies in which patients received ALIMTA with cisplatin were: 2.1% in Study JMDB and 2.2% in Study JMCH. The incidence of renal failure in clinical studies in which patients received ALIMTA as a single agent ranged from 0.4% to 0.6% (Studies JMEN, PARAMOUNT, and JMEI [see Adverse Reactions (6.1)]. Determine creatinine clearance before each dose and periodically monitor renal function during treatment with ALIMTA. Withhold ALIMTA in patients with a creatinine clearance of less than 45 mL/minute [see Dosage and Administration (2.3)].

5.3 Bullous and Exfoliative Skin Toxicity

Serious and sometimes fatal, bullous, blistering and exfoliative skin toxicity, including cases suggestive of Stevens-Johnson Syndrome/Toxic epidermal necrolysis can occur with ALIMTA. Permanently discontinue ALIMTA for severe and life-threatening bullous, blistering or exfoliating skin toxicity.

5.4 Interstitial Pneumonitis

Serious interstitial pneumonitis, including fatal cases, can occur with ALIMTA treatment. Withhold ALIMTA for acute onset of new or progressive unexplained pulmonary symptoms such as dyspnea, cough, or fever pending diagnostic evaluation. If pneumonitis is confirmed, permanently discontinue ALIMTA.

5.5 Radiation Recall

Radiation recall can occur with ALIMTA in patients who have received radiation weeks to years previously. Monitor patients for inflammation or blistering in areas of previous radiation treatment. Permanently discontinue ALIMTA for signs of radiation recall.

5.6 Increased Risk of Toxicity with Ibuprofen in Patients with Renal Impairment

Exposure to ALIMTA is increased in patients with mild to moderate renal impairment who take concomitant ibuprofen, increasing the risks of adverse reactions of ALIMTA. In patients with creatinine clearances between 45 mL/min and 79 mL/min, avoid administration of ibuprofen for 2 days before, the day of, and 2 days following administration of ALIMTA. If concomitant ibuprofen use cannot be avoided, monitor patients more frequently for ALIMTA adverse reactions, including myelosuppression, renal, and gastrointestinal toxicity [see Dosage and Administration (2.5), Drug Interactions (7), and Clinical Pharmacology (12.3)].

5.7 Embryo-Fetal Toxicity

Based on findings from animal studies and its mechanism of action, ALIMTA can cause fetal harm when administered to a pregnant woman. In animal reproduction studies, intravenous administration of pemetrexed to pregnant mice during the period of organogenesis was teratogenic, resulting in developmental delays and increased malformations at doses lower than the recommended human dose of 500 mg/m^2. Advise pregnant women of the potential risk to a fetus. Advise females of reproductive potential to use effective contraception during treatment with ALIMTA and for 6 months after the last dose. Advise males with female partners of reproductive potential to use effective contraception during treatment with ALIMTA and for 3 months after the last dose [see Use in Specific Populations (8.1, 8.3) and Clinical Pharmacology (12.1)].

6 ADVERSE REACTIONS

The following adverse reactions are discussed in greater detail in other sections of the labeling:

- Myelosuppression [see Warnings and Precautions (5.1)]
- Renal failure [see Warnings and Precautions (5.2)]
- Bullous and exfoliative skin toxicity [see Warning and Precautions (5.3)]
- Interstitial pneumonitis [see Warnings and Precautions (5.4)]
- Radiation recall [see Warnings and Precautions (5.5)]

6.1 Clinical Trials Experience

Because clinical trials are conducted under widely varying conditions, adverse reactions rates cannot be directly compared to rates in other clinical trials and may not reflect the rates observed in clinical practice.

In clinical trials, the most common adverse reactions (incidence ≥20%) of ALIMTA, when administered as a single agent, are fatigue, nausea, and anorexia. The most common adverse reactions (incidence ≥20%) of ALIMTA, when administered in combination with cisplatin are vomiting, neutropenia, anemia, stomatitis/pharyngitis, thrombocytopenia, and constipation. The most common adverse reactions (incidence ≥20%) of ALIMTA, when administered in combination with pembrolizumab and platinum chemotherapy, are fatigue/asthenia, nausea, constipation, diarrhea, decreased appetite, rash, vomiting, cough, dyspnea, and pyrexia.

Non-Squamous NSCLC

First-line Treatment of Metastatic Non-squamous NSCLC with Pembrolizumab and Platinum Chemotherapy

The safety of ALIMTA, in combination with pembrolizumab and investigator's choice of platinum (either carboplatin or cisplatin), was investigated in Study KEYNOTE-189, a multicenter, double-blind, randomized (2:1), active-controlled trial in patients with previously untreated, metastatic non-squamous NSCLC with no EGFR or ALK genomic tumor aberrations. A total of 607 patients received ALIMTA, pembrolizumab, and platinum every 3 weeks for 4 cycles followed by ALIMTA and pembrolizumab (n=405), or placebo, ALIMTA, and platinum every 3 weeks for 4 cycles followed by placebo and ALIMTA (n=202). Patients with autoimmune disease that required systemic therapy within 2 years of treatment; a medical condition that required immunosuppression; or who had received more than 30 Gy of thoracic radiation within the prior 26 weeks were ineligible [see Clinical Studies (14.1)].

The median duration of exposure to ALIMTA was 7.2 months (range: 1 day to 1.7 years). Seventy-two percent of patients received carboplatin. The study population characteristics were: median age of 64 years (range: 34 to 84), 49% age 65 years or older, 59% male, 94% White and 3% Asian, and 18% with history of brain metastases at baseline.

ALIMTA was discontinued for adverse reactions in 23% of patients in the ALIMTA, pembrolizumab, and platinum arm. The most common adverse reactions resulting in discontinuation of ALIMTA in this arm were acute kidney injury (3%) and pneumonitis (2%). Adverse reactions leading to interruption of ALIMTA occurred in 49% of patients in the ALIMTA, pembrolizumab, and platinum arm. The most common adverse reactions or laboratory abnormalities leading to interruption of ALIMTA in this arm (≥2%) were neutropenia (12%), anemia (7%), asthenia (4%), pneumonia (4%), thrombocytopenia (4%), increased blood creatinine (3%), diarrhea (3%), and fatigue (3%).

Table 2 summarizes the adverse reactions that occurred in ≥20% of patients treated with ALIMTA, pembrolizumab, and platinum.

Table 2: Adverse Reactions Occurring in ≥20% of Patients in KEYNOTE-189
 | ALIMTA Pembrolizumab Platinum Chemotherapy n=405 |  |  | Placebo ALIMTA Platinum Chemotherapy n=202
Adverse Reaction | All Gradesa (%) |  | Grade 3-4 (%) | All Grades (%) | Grade 3-4 (%)
Gastrointestinal Disorders
Nausea | 56 |  | 3.5 | 52 | 3.5
Constipation | 35 |  | 1.0 | 32 | 0.5
Diarrhea | 31 |  | 5 | 21 | 3.0
Vomiting | 24 |  | 3.7 | 23 | 3.0
General Disorders and Administration Site Conditions
Fatigueb | 56 |  | 12 | 58 | 6
Pyrexia | 20 |  | 0.2 | 15 | 0
Metabolism and Nutrition Disorders
Decreased appetite |  | 28 | 1.5 | 30 | 0.5
Skin and Subcutaneous Tissue Disorders
Rashc | 25 |  | 2.0 | 17 | 2.5
Respiratory, Thoracic and Mediastinal Disorders
Cough | 21 |  | 0 | 28 | 0
Dyspnea | 21 |  | 3.7 | 26 | 5
a Graded per NCI CTCAE version 4.03.
b Includes asthenia and fatigue.
c Includes genital rash, rash, rash generalized, rash macular, rash maculo-papular, rash papular, rash pruritic, and rash pustular.

Table 3 summarizes the laboratory abnormalities that worsened from baseline in at least 20% of patients treated with ALIMTA, pembrolizumab, and platinum.

Table 3: Laboratory Abnormalities Worsened from Baseline in ≥20% of Patients in KEYNOTE-189
 | ALIMTA Pembrolizumab Platinum Chemotherapy |  | Placebo ALIMTA Platinum Chemotherapy
Laboratory Testa | All Gradesb % | Grades 3-4 % | All Grades % | Grades 3-4 %
Chemistry
Hyperglycemia | 63 | 9 | 60 | 7
Increased ALT | 47 | 3.8 | 42 | 2.6
Increased AST | 47 | 2.8 | 40 | 1.0
Hypoalbuminemia | 39 | 2.8 | 39 | 1.1
Increased creatinine | 37 | 4.2 | 25 | 1.0
Hyponatremia | 32 | 7 | 23 | 6
Hypophosphatemia | 30 | 10 | 28 | 14
Increased alkaline phosphatase | 26 | 1.8 | 29 | 2.1
Hypocalcemia | 24 | 2.8 | 17 | 0.5
Hyperkalemia | 24 | 2.8 | 19 | 3.1
Hypokalemia | 21 | 5 | 20 | 5
Hematology
Anemia | 85 | 17 | 81 | 18
Lymphopenia | 64 | 22 | 64 | 25
Neutropenia | 48 | 20 | 41 | 19
Thrombocytopenia | 30 | 12 | 29 | 8
a Each test incidence is based on the number of patients who had both baseline and at least one on-study laboratory measurement available: ALIMTA/pembrolizumab/platinum chemotherapy (range: 381 to 401 patients) and placebo/ALIMTA/platinum chemotherapy (range: 184 to 197 patients).
b Graded per NCI CTCAE version 4.03.

Initial Treatment in Combination with Cisplatin

The safety of ALIMTA was evaluated in Study JMDB, a randomized (1:1), open-label, multicenter trial conducted in chemotherapy-naive patients with locally advanced or metastatic NSCLC. Patients received either ALIMTA 500 mg/m^2 intravenously and cisplatin 75 mg/m^2 intravenously on Day 1 of each 21-day cycle (n=839) or gemcitabine 1250 mg/m^2 intravenously on Days 1 and 8 and cisplatin 75 mg/m^2 intravenously on Day 1 of each 21-day cycle (n=830). All patients were fully supplemented with folic acid and vitamin B12.

Study JMDB excluded patients with an Eastern Cooperative Oncology Group Performance Status (ECOG PS of 2 or greater), uncontrolled third-space fluid retention, inadequate bone marrow reserve and organ function, or a calculated creatinine clearance less than 45 mL/min. Patients unable to stop using aspirin or other non-steroidal anti-inflammatory drugs or unable to take folic acid, vitamin B12 or corticosteroids were also excluded from the study.

The data described below reflect exposure to ALIMTA plus cisplatin in 839 patients in Study JMDB. Median age was 61 years (range 26-83 years); 70% of patients were men; 78% were White, 16% were Asian, 2.9% were Hispanic or Latino, 2.1% were Black or African American, and <1% were other ethnicities; 36% had an ECOG PS 0. Patients received a median of 5 cycles of ALIMTA.

Table 4 provides the frequency and severity of adverse reactions that occurred in ≥5% of 839 patients receiving ALIMTA in combination with cisplatin in Study JMDB. Study JMDB was not designed to demonstrate a statistically significant reduction in adverse reaction rates for ALIMTA, as compared to the control arm, for any specified adverse reaction listed in Table 4.

Table 4: Adverse Reactions Occurring in ≥5% of Fully Vitamin-Supplemented Patients Receiving ALIMTA in Combination with Cisplatin Chemotherapy in Study JMDB
Adverse Reactiona | ALIMTA/Cisplatin (N=839) |  | Gemcitabine/Cisplatin (N=830)
Adverse Reactiona | All Grades (%) | Grade 3-4 (%) | All Grades (%) | Grade 3-4 (%)
All adverse reactions | 90 | 37 | 91 | 53
Laboratory
Hematologic
Anemia | 33 | 6 | 46 | 10
Neutropenia | 29 | 15 | 38 | 27
Thrombocytopenia | 10 | 4 | 27 | 13
Renal
Elevated creatinine | 10 | 1 | 7 | 1
Clinical
Constitutional symptoms
Fatigue | 43 | 7 | 45 | 5
Gastrointestinal
Nausea | 56 | 7 | 53 | 4
Vomiting | 40 | 6 | 36 | 6
Anorexia | 27 | 2 | 24 | 1
Constipation | 21 | 1 | 20 | 0
Stomatitis/pharyngitis | 14 | 1 | 12 | 0
Diarrhea | 12 | 1 | 13 | 2
Dyspepsia/heartburn | 5 | 0 | 6 | 0
Neurology
Sensory neuropathy | 9 | 0 | 12 | 1
Taste disturbance | 8 | 0 | 9 | 0
Dermatology/Skin
Alopecia | 12 | 0 | 21 | 1
Rash/Desquamation | 7 | 0 | 8 | 1
a NCI CTCAE version 2.0.

The following additional adverse reactions of ALIMTA were observed.

Incidence 1% to <5%
Body as a Whole — febrile neutropenia, infection, pyrexia
General Disorders — dehydration
Metabolism and Nutrition — increased AST, increased ALT
Renal —renal failure
Eye Disorder — conjunctivitis
Incidence <1%
Cardiovascular — arrhythmia
General Disorders — chest pain
Metabolism and Nutrition — increased GGT
Neurology — motor neuropathy

Maintenance Treatment Following First-line Non-ALIMTA Containing Platinum-Based Chemotherapy

In Study JMEN, the safety of ALIMTA was evaluated in a randomized (2:1), placebo-controlled, multicenter trial conducted in patients with non-progressive locally advanced or metastatic NSCLC following four cycles of a first-line, platinum-based chemotherapy regimen. Patients received either ALIMTA 500 mg/m^2 or matching placebo intravenously every 21 days until disease progression or unacceptable toxicity. Patients in both study arms were fully supplemented with folic acid and vitamin B12.

Study JMEN excluded patients with an ECOG PS of 2 or greater, uncontrolled third-space fluid retention, inadequate bone marrow reserve and organ function, or a calculated creatinine clearance less than 45 mL/min. Patients unable to stop using aspirin or other non-steroidal anti-inflammatory drugs or unable to take folic acid, vitamin B12 or corticosteroids were also excluded from the study.

The data described below reflect exposure to ALIMTA in 438 patients in Study JMEN. Median age was 61 years (range 26-83 years), 73% of patients were men; 65% were White, 31% were Asian, 2.9% were Hispanic or Latino, and <2% were other ethnicities; 39% had an ECOG PS 0. Patients received a median of 5 cycles of ALIMTA and a relative dose intensity of ALIMTA of 96%. Approximately half the patients (48%) completed at least six, 21-day cycles and 23% completed ten or more 21-day cycles of ALIMTA.

Table 5 provides the frequency and severity of adverse reactions reported in ≥5% of the 438 ALIMTA-treated patients in Study JMEN.

Table 5: Adverse Reactions Occurring in ≥5% of Patients Receiving ALIMTA in Study JMEN
Adverse Reactiona | ALIMTA (N=438) |  | Placebo (N=218)
Adverse Reactiona | All Grades (%) | Grade 3-4 (%) | All Grades (%) | Grade 3-4 (%)
All adverse reactions | 66 | 16 | 37 | 4
Laboratory
Hematologic
Anemia | 15 | 3 | 6 | 1
Neutropenia | 6 | 3 | 0 | 0
Hepatic
Increased ALT | 10 | 0 | 4 | 0
Increased AST | 8 | 0 | 4 | 0
Clinical
Constitutional symptoms
Fatigue | 25 | 5 | 11 | 1
Gastrointestinal
Nausea | 19 | 1 | 6 | 1
Anorexia | 19 | 2 | 5 | 0
Vomiting | 9 | 0 | 1 | 0
Mucositis/stomatitis | 7 | 1 | 2 | 0
Diarrhea | 5 | 1 | 3 | 0
Infection | 5 | 2 | 2 | 0
Neurology
Sensory neuropathy | 9 | 1 | 4 | 0
Dermatology/Skin
Rash/desquamation | 10 | 0 | 3 | 0
a NCI CTCAE version 3.0.

The requirement for transfusions (9.5% versus 3.2%), primarily red blood cell transfusions, and for erythropoiesis stimulating agents (5.9% versus 1.8%) were higher in the ALIMTA arm compared to the placebo arm.

The following additional adverse reactions were observed in patients who received ALIMTA.

Incidence 1% to<5%
Dermatology/Skin — alopecia, pruritus/itching
Gastrointestinal — constipation
General Disorders — edema, fever
Hematologic — thrombocytopenia
Eye Disorder — ocular surface disease (including conjunctivitis), increased lacrimation
Incidence <1%
Cardiovascular — supraventricular arrhythmia
Dermatology/Skin — erythema multiforme
General Disorders — febrile neutropenia, allergic reaction/hypersensitivity
Neurology — motor neuropathy
Renal — renal failure

Maintenance Treatment Following First-line ALIMTA Plus Platinum Chemotherapy

The safety of ALIMTA was evaluated in PARAMOUNT, a randomized (2:1), placebo-controlled study conducted in patients with non-squamous NSCLC with non-progressive (stable or responding disease) locally advanced or metastatic NSCLC following four cycles of ALIMTA in combination with cisplatin as first-line therapy for NSCLC. Patients were randomized to receive ALIMTA 500 mg/m^2 or matching placebo intravenously on Day 1 of each 21-day cycle until disease progression or unacceptable toxicity. Patients in both study arms received folic acid and vitamin B12 supplementation.

PARAMOUNT excluded patients with an ECOG PS of 2 or greater, uncontrolled third-space fluid retention, inadequate bone marrow reserve and organ function, or a calculated creatinine clearance less than 45 mL/min. Patients unable to stop using aspirin or other non-steroidal anti-inflammatory drugs or unable to take folic acid, vitamin B12 or corticosteroids were also excluded from the study.

The data described below reflect exposure to ALIMTA in 333 patients in PARAMOUNT. Median age was 61 years (range 32 to 83 years); 58% of patients were men; 94% were White, 4.8% were Asian, and <1% were Black or African American; 36% had an ECOG PS 0. The median number of maintenance cycles was 4 for ALIMTA and placebo arms. Dose reductions for adverse reactions occurred in 3.3% of patients in the ALIMTA arm and 0.6% in the placebo arm. Dose delays for adverse reactions occurred in 22% of patients in the ALIMTA arm and 16% in the placebo arm.

Table 6 provides the frequency and severity of adverse reactions reported in ≥5% of the 333 ALIMTA-treated patients in PARAMOUNT.

Table 6: Adverse Reactions Occurring in ≥5% of Patients Receiving ALIMTA in PARAMOUNT
Adverse Reactiona | ALIMTA (N=333) |  | Placebo (N=167)
Adverse Reactiona | All Grades (%) | Grade 3-4 (%) | All Grades (%) | Grades 3-4 (%)
All adverse reactions | 53 | 17 | 34 | 4.8
Laboratory
Hematologic
Anemia | 15 | 4.8 | 4.8 | 0.6
Neutropenia | 9 | 3.9 | 0.6 | 0
Clinical
Constitutional symptoms
Fatigue | 18 | 4.5 | 11 | 0.6
Gastrointestinal
Nausea | 12 | 0.3 | 2.4 | 0
Vomiting | 6 | 0 | 1.8 | 0
Mucositis/stomatitis | 5 | 0.3 | 2.4 | 0
General disorders
Edema | 5 | 0 | 3.6 | 0
a NCI CTCAE version 3.0.

The requirement for red blood cell (13% versus 4.8%) and platelet (1.5% versus 0.6%) transfusions, erythropoiesis stimulating agents (12% versus 7%), and granulocyte colony stimulating factors (6% versus 0%) were higher in the ALIMTA arm compared to the placebo arm.

The following additional Grade 3 or 4 adverse reactions were observed more frequently in the ALIMTA arm.

Incidence 1% to <5%
Blood/Bone Marrow — thrombocytopenia
General Disorders — febrile neutropenia
Incidence <1%
Cardiovascular — ventricular tachycardia, syncope
General Disorders — pain
Gastrointestinal — gastrointestinal obstruction
Neurologic — depression
Renal — renal failure
Vascular — pulmonary embolism

Treatment of Recurrent Disease After Prior Chemotherapy

The safety of ALIMTA was evaluated in Study JMEI, a randomized (1:1), open-label, active-controlled trial conducted in patients who had progressed following platinum-based chemotherapy. Patients received ALIMTA 500 mg/m^2 intravenously or docetaxel 75 mg/m^2 intravenously on Day 1 of each 21-day cycle. All patients on the ALIMTA arm received folic acid and vitamin B12 supplementation.

Study JMEI excluded patients with an ECOG PS of 3 or greater, uncontrolled third-space fluid retention, inadequate bone marrow reserve and organ function, or a calculated creatinine clearance less than 45 mL/min. Patients unable to discontinue aspirin or other non-steroidal anti-inflammatory drugs or unable to take folic acid, vitamin B12 or corticosteroids were also excluded from the study.

The data described below reflect exposure to ALIMTA in 265 patients in Study JMEI. Median age was 58 years (range 22 to 87 years); 73% of patients were men; 70% were White, 24% were Asian, 2.6% were Black or African American, 1.8% were Hispanic or Latino, and <2% were other ethnicities; 19% had an ECOG PS 0.

Table 7 provides the frequency and severity of adverse reactions reported in ≥5% of the 265 ALIMTA-treated patients in Study JMEI. Study JMEI is not designed to demonstrate a statistically significant reduction in adverse reaction rates for ALIMTA, as compared to the control arm, for any specified adverse reaction listed in the Table 7 below.

Table 7: Adverse Reactions Occurring in ≥5% of Fully Supplemented Patients Receiving ALIMTA in Study JMEI
Adverse Reactiona | ALIMTA (N=265) |  | Docetaxel (N=276)
Adverse Reactiona | All Grades (%) | Grades 3-4 (%) | All Grade (%) | Grades 3-4 (%)
Laboratory
Hematologic
Anemia | 19 | 4 | 22 | 4
Neutropenia | 11 | 5 | 45 | 40
Thrombocytopenia | 8 | 2 | 1 | 0
Hepatic
Increased ALT | 8 | 2 | 1 | 0
Increased AST | 7 | 1 | 1 | 0
Clinical
Gastrointestinal
Nausea | 31 | 3 | 17 | 2
Anorexia | 22 | 2 | 24 | 3
Vomiting | 16 | 2 | 12 | 1
Stomatitis/pharyngitis | 15 | 1 | 17 | 1
Diarrhea | 13 | 0 | 24 | 3
Constipation | 6 | 0 | 4 | 0
Constitutional symptoms
Fatigue | 34 | 5 | 36 | 5
Fever | 8 | 0 | 8 | 0
Dermatology/Skin
Rash/desquamation | 14 | 0 | 6 | 0
Pruritus | 7 | 0 | 2 | 0
Alopecia | 6 | 1 | 38 | 2
a NCI CTCAE version 2.0.

The following additional adverse reactions were observed in patients assigned to receive ALIMTA.

Incidence 1% to <5%
Body as a Whole — abdominal pain, allergic reaction/hypersensitivity, febrile neutropenia, infection
Dermatology/Skin — erythema multiforme
Neurology — motor neuropathy, sensory neuropathy
Incidence <1%
Cardiovascular — supraventricular arrhythmias
Renal — renal failure

Mesothelioma

The safety of ALIMTA was evaluated in Study JMCH, a randomized (1:1), single-blind study conducted in patients with MPM who had received no prior chemotherapy for MPM. Patients received ALIMTA 500 mg/m^2 intravenously in combination with cisplatin 75 mg/m^2 intravenously on Day 1 of each 21-day cycle or cisplatin 75 mg/m^2 intravenously on Day 1 of each 21-day cycle administered until disease progression or unacceptable toxicity. Safety was assessed in 226 patients who received at least one dose of ALIMTA in combination with cisplatin and 222 patients who received at least one dose of cisplatin alone. Among 226 patients who received ALIMTA in combination with cisplatin, 74% (n=168) received full supplementation with folic acid and vitamin B12 during study therapy, 14% (n=32) were never supplemented, and 12% (n=26) were partially supplemented.

Study JMCH excluded patients with Karnofsky Performance Scale (KPS) of less than 70, inadequate bone marrow reserve and organ function, or a calculated creatinine clearance less than 45 mL/min. Patients unable to stop using aspirin or other non-steroidal anti-inflammatory drugs were also excluded from the study.

The data described below reflect exposure to ALIMTA in 168 patients that were fully supplemented with folic acid and vitamin B12. Median age was 60 years (range 19 to 85 years); 82% were men; 92% were White, 5% were Hispanic or Latino, 3.0% were Asian, and <1% were other ethnicities; 54% had KPS of 90-100. The median number of treatment cycles administered was 6 in the ALIMTA/cisplatin fully supplemented group and 2 in the ALIMTA/cisplatin never supplemented group. Patients receiving ALIMTA in the fully supplemented group had a relative dose intensity of 93% of the protocol-specified ALIMTA dose intensity. The most common adverse reaction resulting in dose delay was neutropenia.

Table 8 provides the frequency and severity of adverse reactions ≥5% in the subgroup of ALIMTA-treated patients who were fully vitamin supplemented in Study JMCH. Study JMCH was not designed to demonstrate a statistically significant reduction in adverse reaction rates for ALIMTA, as compared to the control arm, for any specified adverse reaction listed in the table below.

Table 8: Adverse Reactions Occurring in ≥5% of Fully Supplemented Subgroup of Patients Receiving ALIMTA/Cisplatin in Study JMCHa
Adverse Reactionb | ALIMTA/cisplatin (N=168) |  | Cisplatin (N=163)
Adverse Reactionb | All Grades (%) | Grade 3-4 (%) | All Grades (%) | Grade 3-4 (%)
Laboratory
Hematologic
Neutropenia | 56 | 23 | 13 | 3
Anemia | 26 | 4 | 10 | 0
Thrombocytopenia | 23 | 5 | 9 | 0
Renal
Elevated creatinine | 11 | 1 | 10 | 1
Decreased creatinine clearance | 16 | 1 | 18 | 2
Clinical
Eye Disorder
Conjunctivitis | 5 | 0 | 1 | 0
Gastrointestinal
Nausea | 82 | 12 | 77 | 6
Vomiting | 57 | 11 | 50 | 4
Stomatitis/pharyngitis | 23 | 3 | 6 | 0
Anorexia | 20 | 1 | 14 | 1
Diarrhea | 17 | 4 | 8 | 0
Constipation | 12 | 1 | 7 | 1
Dyspepsia | 5 | 1 | 1 | 0
Constitutional Symptoms
Fatigue | 48 | 10 | 42 | 9
Metabolism and Nutrition
Dehydration | 7 | 4 | 1 | 1
Neurology
Sensory neuropathy | 10 | 0 | 10 | 1
Taste disturbance | 8 | 0 | 6 | 0
Dermatology/Skin
Rash | 16 | 1 | 5 | 0
Alopecia | 11 | 0 | 6 | 0
a In Study JMCH, 226 patients received at least one dose of ALIMTA in combination with cisplatin and 222 patients received at least one dose of cisplatin. Table 8 provides the ADRs for subgroup of patients treated with ALIMTA in combination with cisplatin (168 patients) or cisplatin alone (163 patients) who received full supplementation with folic acid and vitamin B12 during study therapy.
b NCI CTCAE version 2.0.

The following additional adverse reactions were observed in patients receiving ALIMTA plus cisplatin:

Incidence 1% to <5%
Body as a Whole — febrile neutropenia, infection, pyrexia
Dermatology/Skin — urticaria
General Disorders — chest pain
Metabolism and Nutrition — increased AST, increased ALT, increased GGT
Renal — renal failure
Incidence <1%
Cardiovascular — arrhythmia
Neurology — motor neuropathy

Exploratory Subgroup Analyses based on Vitamin Supplementation

Table 9 provides the results of exploratory analyses of the frequency and severity of NCI CTCAE Grade 3 or 4 adverse reactions reported in more ALIMTA-treated patients who did not receive vitamin supplementation (never supplemented) as compared with those who received vitamin supplementation with daily folic acid and vitamin B12 from the time of enrollment in Study JMCH (fully-supplemented).

Table 9: Exploratory Subgroup Analysis of Selected Grade 3/4 Adverse Reactions Occurring in Patients Receiving ALIMTA in Combination with Cisplatin with or without Full Vitamin Supplementation in Study JMCHa
Grade 3-4 Adverse Reactions | Fully Supplemented Patients N=168 (%) | Never Supplemented Patients N=32 (%)
Neutropenia | 23 | 38
Thrombocytopenia | 5 | 9
Vomiting | 11 | 31
Febrile neutropenia | 1 | 9
Infection with Grade 3/4 neutropenia | 0 | 6
Diarrhea | 4 | 9
a NCI CTCAE version 2.0.

The following adverse reactions occurred more frequently in patients who were fully vitamin supplemented than in patients who were never supplemented:

- hypertension (11% versus 3%),
- chest pain (8% versus 6%),
- thrombosis/embolism (6% versus 3%).

Additional Experience Across Clinical Trials

Sepsis, with or without neutropenia, including fatal cases: 1%
Severe esophagitis, resulting in hospitalization: <1%

6.2 Postmarketing Experience

The following adverse reactions have been identified during post-approval use of ALIMTA. Because these reactions are reported voluntarily from a population of uncertain size, it is not always possible to reliably estimate their frequency or establish a causal relationship to drug exposure.

Blood and Lymphatic System — immune-mediated hemolytic anemia
Gastrointestinal — colitis, pancreatitis
General Disorders and Administration Site Conditions — edema
Injury, poisoning, and procedural complications — radiation recall
Respiratory — interstitial pneumonitis
Skin — Serious and fatal bullous skin conditions, Stevens-Johnson syndrome, and toxic epidermal necrolysis

7 DRUG INTERACTIONS

Effects of Ibuprofen on Pemetrexed

Ibuprofen increases exposure (AUC) of pemetrexed [see Clinical Pharmacology (12.3)]. In patients with creatinine clearance between 45 mL/min and 79 mL/min:

- Avoid administration of ibuprofen for 2 days before, the day of, and 2 days following administration of ALIMTA [see Dosage and Administration (2.5)].
- Monitor patients more frequently for myelosuppression, renal, and gastrointestinal toxicity, if concomitant administration of ibuprofen cannot be avoided.

8 USE IN SPECIFIC POPULATIONS

8.1 Pregnancy

Risk Summary

Based on findings from animal studies and its mechanism of action, ALIMTA can cause fetal harm when administered to a pregnant woman [see Clinical Pharmacology (12.1)]. There are no available data on ALIMTA use in pregnant women. In animal reproduction studies, intravenous administration of pemetrexed to pregnant mice during the period of organogenesis was teratogenic, resulting in developmental delays and malformations at doses lower than the recommended human dose of 500 mg/m^2 [see Data]. Advise pregnant women of the potential risk to a fetus [see Use in Special Populations (8.3)].

In the U.S. general population, the estimated background risk of major birth defects and miscarriage in clinically recognized pregnancies is 2 to 4% and 15 to 20%, respectively.

Data

Animal Data

Pemetrexed was teratogenic in mice. Daily dosing of pemetrexed by intravenous injection to pregnant mice during the period of organogenesis increased the incidence of fetal malformations (cleft palate; protruding tongue; enlarged or misshaped kidney; and fused lumbar vertebra) at doses (based on BSA) 0.03 times the human dose of 500 mg/m^2. At doses, based on BSA, greater than or equal to 0.0012 times the 500 mg/m^2 human dose, pemetrexed administration resulted in dose-dependent increases in developmental delays (incomplete ossification of talus and skull bone; and decreased fetal weight).

8.2 Lactation

Risk Summary

There is no information regarding the presence of pemetrexed or its metabolites in human milk, the effects on the breastfed infant, or the effects on milk production. Because of the potential for serious adverse reactions in breastfed infants from ALIMTA, advise women not to breastfeed during treatment with ALIMTA and for one week after the last dose.

8.3 Females and Males of Reproductive Potential

Based on animal data ALIMTA can cause malformations and developmental delays when administered to a pregnant woman [see Use in Specific Populations (8.1)].

Pregnancy Testing

Verify pregnancy status of females of reproductive potential prior to initiating Pemetrexed Injection [see Use in Specific Populations (8.1)].

Contraception

Females

Because of the potential for genotoxicity, advise females of reproductive potential to use effective contraception during treatment with ALIMTA and for 6 months after the last dose.

Males

Because of the potential for genotoxicity, advise males with female partners of reproductive potential to use effective contraception during treatment with ALIMTA and for 3 months after the last dose [see Nonclinical Toxicology (13.1)].

Infertility

Males

ALIMTA may impair fertility in males of reproductive potential. It is not known whether these effects on fertility are reversible [see Nonclinical Toxicology (13.1)].

8.4 Pediatric Use

The safety and effectiveness of ALIMTA in pediatric patients have not been established. The safety and pharmacokinetics of ALIMTA were evaluated in two clinical studies conducted in pediatric patients with recurrent solid tumors (NCT00070473 N=32 and NCT00520936 N=72). Patients in both studies received concomitant vitamin B12 and folic acid supplementation and dexamethasone.

No tumor responses were observed. Adverse reactions observed in pediatric patients were similar to those observed in adults.

Single-dose pharmacokinetics of ALIMTA were evaluated in 22 patients age 4 to 18 years enrolled in NCT00070473 were within range of values in adults.

8.5 Geriatric Use

Of the 3,946 patients enrolled in clinical studies of ALIMTA, 34% were 65 and over and 4% were 75 and over. No overall differences in effectiveness were observed between these patients and younger patients. The incidences of Grade 3-4 anemia, fatigue, thrombocytopenia, hypertension, and neutropenia were higher in patients 65 years of age and older as compared to younger patients: in at least one of five randomized clinical trials. [see Adverse Reactions (6.1) and Clinical Studies (14.1, 14.2)].

8.6 Patients with Renal Impairment

ALIMTA is primarily excreted by the kidneys. Decreased renal function results in reduced clearance and greater exposure (AUC) to ALIMTA compared with patients with normal renal function [Warnings and Precautions (5.2, 5.6) and Clinical Pharmacology (12.3)]. No dose is recommended for patients with creatinine clearance less than 45 mL/min [see Dosage and Administration (2.3)].

10 OVERDOSAGE

No drugs are approved for the treatment of ALIMTA overdose. Based on animal studies, administration of leucovorin may mitigate the toxicities of ALIMTA overdosage. It is not known whether pemetrexed is dialyzable.

11 DESCRIPTION

ALIMTA (pemetrexed for injection) is a folate analog metabolic inhibitor. The drug substance, pemetrexed disodium heptahydrate, has the chemical name L-glutamic acid, N-[4-[2-(2-amino-4,7-dihydro-4-oxo-1H-pyrrolo[2,3-d]pyrimidin-5-yl)ethyl]benzoyl]-, disodium salt, heptahydrate with a molecular formula of C20H19N5Na2O6•7H2O and a molecular weight of 597.49. The structural formula is as follows:

ALIMTA is a sterile white-to-light yellow or green-yellow lyophilized powder in single-dose vials to be reconstituted for intravenous infusion. Each 100-mg vial of ALIMTA contains 100 mg pemetrexed (equivalent to 139.8 mg pemetrexed disodium heptahydrate) and 106 mg mannitol. Each 500-mg vial of ALIMTA contains 500 mg pemetrexed (equivalent to 699 mg pemetrexed disodium heptahydrate) and 500 mg mannitol. Hydrochloric acid and/or sodium hydroxide may have been added to adjust pH.

12 CLINICAL PHARMACOLOGY

12.1 Mechanism of Action

ALIMTA is a folate analog metabolic inhibitor that disrupts folate-dependent metabolic processes essential for cell replication. In vitro studies show that pemetrexed inhibits thymidylate synthase (TS), dihydrofolate reductase, and glycinamide ribonucleotide formyltransferase (GARFT), which are folate-dependent enzymes involved in the de novo biosynthesis of thymidine and purine nucleotides. Pemetrexed is taken into cells by membrane carriers such as the reduced folate carrier and membrane folate binding protein transport systems. Once in the cell, pemetrexed is converted to polyglutamate forms by the enzyme folylpolyglutamate synthetase. The polyglutamate forms are retained in cells and are inhibitors of TS and GARFT.

12.2 Pharmacodynamics

Pemetrexed inhibited the in vitro growth of mesothelioma cell lines (MSTO-211H, NCI-H2052) and showed synergistic effects when combined with cisplatin.

Based on population pharmacodynamic analyses, the depth of the absolute neutrophil counts (ANC) nadir correlates with the systemic exposure to pemetrexed and supplementation with folic acid and vitamin B12. There is no cumulative effect of pemetrexed exposure on ANC nadir over multiple treatment cycles.

12.3 Pharmacokinetics

Absorption

The pharmacokinetics of pemetrexed when ALIMTA was administered as a single agent in doses ranging from 0.2 to 838 mg/m^2 infused over a 10-minute period have been evaluated in 426 cancer patients with a variety of solid tumors. Pemetrexed total systemic exposure (AUC) and maximum plasma concentration (Cmax) increased proportionally with increase of dose. The pharmacokinetics of pemetrexed did not change over multiple treatment cycles.

Distribution

Pemetrexed has a steady-state volume of distribution of 16.1 liters. In vitro studies indicated that pemetrexed is 81% bound to plasma proteins.

Elimination

The total systemic clearance of pemetrexed is 91.8 mL/min and the elimination half-life of pemetrexed is 3.5 hours in patients with normal renal function (creatinine clearance of 90 mL/min). As renal function decreases, the clearance of pemetrexed decreases and exposure (AUC) of pemetrexed increases.

Metabolism

Pemetrexed is not metabolized to an appreciable extent.

Excretion

Pemetrexed is primarily eliminated in the urine, with 70% to 90% of the dose recovered unchanged within the first 24 hours following administration. In vitro studies indicated that pemetrexed is a substrate of OAT3 (organic anion transporter 3), a transporter that is involved in the active secretion of pemetrexed.

Specific Populations

Age (26 to 80 years) and sex had no clinically meaningful effect on the systemic exposure of pemetrexed based on population pharmacokinetic analyses.

Racial Groups

The pharmacokinetics of pemetrexed were similar in Whites and Blacks or African Americans. Insufficient data are available for other ethnic groups.

Patients with Hepatic Impairment

Pemetrexed has not been formally studied in patients with hepatic impairment. No effect of elevated AST, ALT, or total bilirubin on the PK of pemetrexed was observed in clinical studies.

Patients with Renal Impairment

Pharmacokinetic analyses of pemetrexed included 127 patients with impaired renal function. Plasma clearance of pemetrexed decreases as renal function decreases, with a resultant increase in systemic exposure. Patients with creatinine clearances of 45, 50, and 80 mL/min had 65%, 54%, and 13% increases, respectively in systemic exposure (AUC) compared to patients with creatinine clearance of 100 mL/min [see Dosage and Administration (2.3) and Warnings and Precautions (5.2)].

Third-Space Fluid

The pemetrexed plasma concentrations in patients with various solid tumors with stable, mild to moderate third-space fluid were comparable to those observed in patients without third space fluid collections. The effect of severe third space fluid on pharmacokinetics is not known.

Drug Interaction Studies

Drugs Inhibiting OAT3 Transporter

Ibuprofen, an OAT3 inhibitor, administered at 400 mg four times a day decreased the clearance of pemetrexed and increased its exposure (AUC) by approximately 20% in patients with normal renal function (creatinine clearance >80 mL/min).

In Vitro Studies

Pemetrexed is a substrate for OAT3. Ibuprofen, an OAT3 inhibitor inhibited the uptake of pemetrexed in OAT3-expressing cell cultures with an average [Iu]/IC50 ratio of 0.38. In vitro data predict that at clinically relevant concentrations, other NSAIDs (naproxen, diclofenac, celecoxib) would not inhibit the uptake of pemetrexed by OAT3 and would not increase the AUC of pemetrexed to a clinically significant extent. [see Drug Interactions (7)].

Pemetrexed is a substrate for OAT4. In vitro, ibuprofen and other NSAIDs (naproxen, diclofenac, celecoxib) are not inhibitors of OAT4 at clinically relevant concentrations.

Aspirin

Aspirin, administered in low to moderate doses (325 mg every 6 hours), does not affect the pharmacokinetics of pemetrexed.

Cisplatin

Cisplatin does not affect the pharmacokinetics of pemetrexed and the pharmacokinetics of total platinum are unaltered by pemetrexed.

Vitamins

Neither folic acid nor vitamin B12 affect the pharmacokinetics of pemetrexed.

Drugs Metabolized by Cytochrome P450 Enzymes

In vitro studies suggest that pemetrexed does not inhibit the clearance of drugs metabolized by CYP3A, CYP2D6, CYP2C9, and CYP1A2.

13 NONCLINICAL TOXICOLOGY

13.1 Carcinogenesis, Mutagenesis, Impairment of Fertility

No carcinogenicity studies have been conducted with pemetrexed. Pemetrexed was clastogenic in an in vivo micronucleus assay in mouse bone marrow but was not mutagenic in multiple in vitro tests (Ames assay, Chinese Hamster Ovary cell assay).

Pemetrexed administered intraperitoneally at doses of ≥0.1 mg/kg/day to male mice (approximately 0.0006 times the recommended human dose based on BSA) resulted in reduced fertility, hypospermia, and testicular atrophy.

14 CLINICAL STUDIES

14.1 Non-Squamous NSCLC

Initial Treatment in Combination with Pembrolizumab and Platinum

The efficacy of ALIMTA in combination with pembrolizumab and platinum chemotherapy was investigated in Study KEYNOTE-189 (NCT02578680), a randomized, multicenter, double-blind, active-controlled trial conducted in patients with metastatic non-squamous NSCLC, regardless of PD-L1 tumor expression status, who had not previously received systemic therapy for metastatic disease and in whom there were no EGFR or ALK genomic tumor aberrations. Patients with autoimmune disease that required systemic therapy within 2 years of treatment; a medical condition that required immunosuppression; or who had received more than 30 Gy of thoracic radiation within the prior 26 weeks were ineligible. Randomization was stratified by smoking status (never versus former/current), choice of platinum (cisplatin versus carboplatin), and tumor PD-L1 status (TPS <1% [negative] versus TPS ≥1%). Patients were randomized (2:1) to one of the following treatment arms:

- ALIMTA 500 mg/m^2, pembrolizumab 200 mg, and investigator's choice of cisplatin 75 mg/m^2 or carboplatin AUC 5 mg/mL/min intravenously on Day 1 of each 21-day cycle for 4 cycles followed by ALIMTA 500 mg/m^2 and pembrolizumab 200 mg intravenously every 3 weeks. ALIMTA was administered after pembrolizumab and prior to platinum chemotherapy on Day 1.
- Placebo, ALIMTA 500 mg/m^2, and investigator's choice of cisplatin 75 mg/m^2 or carboplatin AUC 5 mg/mL/min intravenously on Day 1 of each 21-day cycle for 4 cycles followed by placebo and ALIMTA 500 mg/m^2 intravenously every 3 weeks.

Treatment with ALIMTA continued until RECIST v1.1 (modified to follow a maximum of 10 target lesions and a maximum of 5 target lesions per organ)-defined progression of disease as determined by the investigator or unacceptable toxicity.

Patients randomized to placebo, ALIMTA, and platinum chemotherapy were offered pembrolizumab as a single agent at the time of disease progression.

Assessment of tumor status was performed at Week 6, Week 12, and then every 9 weeks thereafter. The main efficacy outcome measures were OS and PFS as assessed by BICR RECIST v1.1, modified to follow a maximum of 10 target lesions and a maximum of five target lesions per organ. Additional efficacy outcome measures were ORR and duration of response, as assessed by the BICR according to RECIST v1.1, modified to follow a maximum of 10 target lesions and a maximum of 5 target lesions per organ.

A total of 616 patients were randomized: 410 patients to the ALIMTA, pembrolizumab, and platinum chemotherapy arm and 206 to the placebo, ALIMTA, and platinum chemotherapy arm. The study population characteristics were: median age of 64 years (range: 34 to 84); 49% age 65 or older; 59% male; 94% White and 3% Asian; 56% ECOG performance status of 1; and 18% with history of brain metastases. Thirty-one percent had tumor PD-L1 expression TPS <1%. Seventy-two percent received carboplatin and 12% were never smokers. A total of 85 patients in the placebo, ALIMTA, and chemotherapy arm received an anti-PD-1/PD-L1 monoclonal antibody at the time of disease progression.

The trial demonstrated a statistically significant improvement in OS and PFS for patients randomized to ALIMTA in combination with pembrolizumab and platinum chemotherapy compared with placebo, ALIMTA, and platinum chemotherapy (see Table 10 and Figure 1).

Table 10: Efficacy Results of KEYNOTE-189
Endpoint | ALIMTA Pembrolizumab Platinum Chemotherapy n=410 | Placebo ALIMTA Platinum Chemotherapy n=206
OS
Number (%) of patients with event | 127 (31%) | 108 (52%)
Median in months (95% CI) | NR (NR, NR) | 11.3 (8.7, 15.1)
Hazard ratioa (95% CI) | 0.49 (0.38, 0.64)
p-valueb | <0.0001
PFS
Number of patients with event (%) | 245 (60%) | 166 (81%)
Median in months (95% CI) | 8.8 (7.6, 9.2) | 4.9 (4.7, 5.5)
Hazard ratioa (95% CI) | 0.52 (0.43, 0.64)
p-valueb | <0.0001
ORR
Overall response ratec (95% CI) | 48% (43, 53) | 19% (14, 25)
Complete response | 0.5% | 0.5%
Partial response | 47% | 18%
p-valued | <0.0001
Duration of Response
Median in months (range) | 11.2 (1.1+, 18.0+) | 7.8 (2.1+, 16.4+)
a Based on the stratified Cox proportional hazard model.
b Based on stratified log-rank test.
c Response: Best objective response as confirmed complete response or partial response.
d Based on Miettinen and Nurminen method stratified by PD-L1 status, platinum chemotherapy and smoking status.
NR = not reached

At the protocol specified final OS analysis, the median in the ALIMTA in combination with pembrolizumab and platinum chemotherapy arm was 22.0 months (95% CI: 19.5, 24.5) compared to 10.6 months (95% CI: 8.7, 13.6) in the placebo with ALIMTA and platinum chemotherapy arm, with an HR of 0.56 (95% CI: 0.46, 0.69).

Figure 1: Kaplan-Meier Curve for Overall Survival in KEYNOTE-189*

*Based on the protocol-specified final OS analysis

Initial Treatment in Combination with Cisplatin

The efficacy of ALIMTA was evaluated in Study JMDB (NCT00087711), a multi-center, randomized (1:1), open-label study conducted in 1725 chemotherapy-naive patients with Stage IIIb/IV NSCLC. Patients were randomized to receive ALIMTA with cisplatin or gemcitabine with cisplatin. Randomization was stratified by Eastern Cooperative Oncology Group Performance Status (ECOG PS 0 versus 1), gender, disease stage, basis for pathological diagnosis (histopathological/cytopathological), history of brain metastases, and investigative center. ALIMTA was administered intravenously over 10 minutes at a dose of 500 mg/m^2 on Day 1 of each 21-day cycle. Cisplatin was administered intravenously at a dose of 75 mg/m^2 approximately 30 minutes after ALIMTA administration on Day 1 of each cycle, gemcitabine was administered at a dose of 1250 mg/m^2 on Day 1 and Day 8, and cisplatin was administered intravenously at a dose of 75 mg/m^2 approximately 30 minutes after administration of gemcitabine, on Day 1 of each 21-day cycle. Treatment was administered up to a total of 6 cycles; patients in both arms received folic acid, vitamin B12, and dexamethasone [see Dosage and Administration (2.4)]. The primary efficacy outcome measure was overall survival.

A total of 1725 patients were enrolled with 862 patients randomized to ALIMTA in combination with cisplatin and 863 patients to gemcitabine in combination with cisplatin. The median age was 61 years (range 26-83 years), 70% were male, 78% were White, 17% were Asian, 2.9% were Hispanic or Latino, and 2.1% were Black or African American, and <1% were other ethnicities. Among patients for whom ECOG PS (n=1722) and smoking history (n=1516) were collected, 65% had an ECOG PS of 1, 36% had an ECOG PS of 0, and 84% were smokers. For tumor characteristics, 73% had non-squamous NSCLC and 27% had squamous NSCLC; 76% had Stage IV disease. Among 1252 patients with non-squamous NSCLC histology, 68% had a diagnosis of adenocarcinoma, 12% had large cell histology and 20% had other histologic subtypes.

Efficacy results in Study JMDB are presented in Table 11 and Figure 2.

Table 11: Efficacy Results in Study JMDB
Efficacy Parameter | ALIMTA plus Cisplatin (N=862) | Gemcitabine plus Cisplatin (N=863)
Overall Survival
Median (months) (95% CI) | 10.3 (9.8-11.2) | 10.3 (9.6-10.9)
Hazard ratio (HR)a,b (95% CI) | 0.94 (0.84-1.05)
Progression-Free Survival
Median (months) (95% CI) | 4.8 (4.6-5.3) | 5.1 (4.6-5.5)
Hazard ratio (HR)a,b (95% CI) | 1.04 (0.94-1.15)
Overall Response Rate (95% CI) | 27.1% (24.2-30.1) | 24.7% (21.8-27.6)
a Unadjusted for multiple comparisons.
b Adjusted for gender, stage, basis of diagnosis, and performance status.

Figure 2: Kaplan-Meier Curves for Overall Survival in Study JMDB

In pre-specified analyses assessing the impact of NSCLC histology on overall survival, clinically relevant differences in survival according to histology were observed. These subgroup analyses are shown in Table 12 and Figures 3 and 4. This difference in treatment effect for ALIMTA based on histology demonstrating a lack of efficacy in squamous cell histology was also observed in Studies JMEN and JMEI.

Table 12: Overall Survival in NSCLC Histologic Subgroups in Study JMDB
Histologic Subgroups | ALIMTA plus Cisplatin (N=862) | Gemcitabine plus Cisplatin (N=863)
Non-squamous NSCLC (N=1252)
Median (months) (95% CI) | 11.0 (10.1-12.5) | 10.1 (9.3-10.9)
HRa,b (95% CI) | 0.84 (0.74-0.96)
Adenocarcinoma (N=847)
Median (months) (95% CI) | 12.6 (10.7-13.6) | 10.9 (10.2-11.9)
HRa,b (95% CI) | 0.84 (0.71-0.99)
Large Cell (N=153)
Median (months) (95% CI) | 10.4 (8.6-14.1) | 6.7 (5.5-9.0)
HRa,b (95% CI) | 0.67 (0.48-0.96)
Non-squamous, not otherwise specified (N=252)
Median (months) (95% CI) | 8.6 (6.8-10.2) | 9.2 (8.1-10.6)
HRa,b (95% CI) | 1.08 (0.81-1.45)
Squamous Cell (N=473)
Median (months) (95% CI) | 9.4 (8.4-10.2) | 10.8 (9.5-12.1)
HRa,b (95% CI) | 1.23 (1.00-1.51)
a Unadjusted for multiple comparisons.
b Adjusted for ECOG PS, gender, disease stage, and basis for pathological diagnosis (histopathological/cytopathological).

Figure 3: Kaplan-Meier Curves for Overall Survival in Non-squamous NSCLC in Study JMDB
Figure 4: Kaplan-Meier Curves for Overall Survival in Squamous NSCLC in Study JMDB

Maintenance Treatment Following First-line Non-ALIMTA Containing Platinum-Based Chemotherapy

The efficacy of ALIMTA as maintenance therapy following first-line platinum-based chemotherapy was evaluated in Study JMEN (NCT00102804), a multicenter, randomized (2:1), double-blind, placebo-controlled study conducted in 663 patients with Stage IIIb/IV NSCLC who did not progress after four cycles of platinum-based chemotherapy. Patients were randomized to receive ALIMTA 500 mg/m^2 intravenously every 21 days or placebo until disease progression or intolerable toxicity. Patients in both study arms received folic acid, vitamin B12, and dexamethasone [see Dosage and Administration (2.4)]. Randomization was carried out using a minimization approach [Pocock and Simon (1975)] using the following factors: gender, ECOG PS (0 versus 1), response to prior chemotherapy (complete or partial response versus stable disease), history of brain metastases (yes versus no), non-platinum component of induction therapy (docetaxel versus gemcitabine versus paclitaxel), and disease stage (IIIb versus IV). The major efficacy outcome measures were progression-free survival based on assessment by independent review and overall survival; both were measured from the date of randomization in Study JMEN.

A total of 663 patients were enrolled with 441 patients randomized to ALIMTA and 222 patients randomized to placebo. The median age was 61 years (range 26-83 years); 73% were male; 65% were White, 32% were Asian, 2.9% were Hispanic or Latino, and <2% were other ethnicities; 60% had an ECOG PS of 1; and 73% were current or former smokers. Median time from initiation of platinum-based chemotherapy to randomization was 3.3 months (range 1.6 to 5.1 months) and 49% of the population achieved a partial or complete response to first-line, platinum-based chemotherapy. With regard to tumor characteristics, 81% had Stage IV disease, 73% had non-squamous NSCLC and 27% had squamous NSCLC. Among the 481 patients with non-squamous NSCLC, 68% had adenocarcinoma, 4% had large cell, and 28% had other histologies.

Efficacy results are presented in Table 13 and Figure 5.

Table 13: Efficacy Results in Study JMEN
Efficacy Parameter | ALIMTA | Placebo
Overall survival | N=441 | N=222
Median (months) (95% CI) | 13.4 (11.9-15.9) | 10.6 (8.7-12.0)
Hazard ratioa (95% CI) | 0.79 (0.65-0.95)
p-value | p=0.012
Progression-free survival per independent review | N=387 | N=194
Median (months) (95% CI) | 4.0 (3.1-4.4) | 2.0 (1.5-2.8)
Hazard ratioa (95% CI) | 0.60 (0.49-0.73)
p-value | p<0.00001
a Hazard ratios are adjusted for multiplicity but not for stratification variables.

Figure 5: Kaplan-Meier Curves for Overall Survival in Study JMEN

The results of pre-specified subgroup analyses by NSCLC histology are presented in Table 14 and Figures 6 and 7.

Table 14: Efficacy Results in Study JMEN by Histologic Subgroup
Efficacy Parameter | Overall Survival |  | Progression-Free Survival Per Independent Review
Efficacy Parameter | ALIMTA (N=441) | Placebo (N=222) | ALIMTA (N=387) | Placebo (N=194)
Non-squamous NSCLC (n=481)
Median (months) | 15.5 | 10.3 | 4.4 | 1.8
HRa | 0.70 |  | 0.47
(95% CI) | (0.56-0.88) |  | (0.37-0.60)
Adenocarcinoma (n=328)
Median (months) | 16.8 | 11.5 | 4.6 | 2.7
HRa | 0.73 |  | 0.51
(95% CI) | (0.56-0.96) |  | (0.38-0.68)
Large cell carcinoma (n=20)
Median (months) | 8.4 | 7.9 | 4.5 | 1.5
HRa | 0.98 |  | 0.40
(95% CI) | (0.36-2.65) |  | (0.12-1.29)
Otherb (n=133)
Median (months) | 11.3 | 7.7 | 4.1 | 1.6
HRa | 0.61 |  | 0.44
(95% CI) | (0.40-0.94) |  | (0.28-0.68)
Squamous cell NSCLC (n=182)
Median (months) | 9.9 | 10.8 | 2.4 | 2.5
HRa | 1.07 |  | 1.03
(95% CI) | (0.77-1.50) |  | (0.71-1.49)
a Hazard ratios are not adjusted for multiplicity
b Primary diagnosis of NSCLC not specified as adenocarcinoma, large cell carcinoma, or squamous cell carcinoma.

Figure 6: Kaplan-Meier Curves for Overall Survival in Non-squamous NSCLC in Study JMEN
Figure 7: Kaplan-Meier Curves for Overall Survival in Squamous NSCLC in Study JMEN

Maintenance Treatment Following First-line ALIMTA Plus Platinum Chemotherapy

The efficacy of ALIMTA as maintenance therapy following first-line platinum-based chemotherapy was also evaluated in PARAMOUNT (NCT00789373), a multi-center, randomized (2:1), double-blind, placebo-controlled study conducted in patients with Stage IIIb/IV non-squamous NSCLC who had completed four cycles of ALIMTA in combination with cisplatin and achieved a complete response (CR) or partial response (PR) or stable disease (SD). Patients were required to have an ECOG PS of 0 or 1. Patients were randomized to receive ALIMTA 500 mg/m^2 intravenously every 21 days or placebo until disease progression. Randomization was stratified by response to ALIMTA in combination with cisplatin induction therapy (CR or PR versus SD), disease stage (IIIb versus IV), and ECOG PS (0 versus 1). Patients in both arms received folic acid, vitamin B12, and dexamethasone. The main efficacy outcome measure was investigator-assessed progression-free survival (PFS) and an additional efficacy outcome measure was overall survival (OS); PFS and OS were measured from the time of randomization.

A total of 539 patients were enrolled with 359 patients randomized to ALIMTA and 180 patients randomized to placebo. The median age was 61 years (range 32 to 83 years); 58% were male; 95% were White, 4.5% were Asian, and <1% were Black or African American; 67% had an ECOG PS of 1; 78% were current or former smokers; and 43% of the population achieved a partial or complete response to first-line, platinum-based chemotherapy. With regard to tumor characteristics, 91% had Stage IV disease, 87% had adenocarcinoma, 7% had large cell, and 6% had other histologies.

Efficacy results for PARAMOUNT are presented in Table 15 and Figure 8.

Table 15: Efficacy Results in PARAMOUNT
Efficacy Parameter | ALIMTA (N=359) | Placebo (N=180)
Overall survival
Median (months) (95% CI) | 13.9 (12.8-16.0) | 11.0 (10.0-12.5)
Hazard ratio (HR)a (95% CI) | 0.78 (0.64-0.96)
p-value | p=0.02
Progression-free survivalb
Median (months) (95% CI) | 4.1 (3.2-4.6) | 2.8 (2.6-3.1)
Hazard ratio (HR)a (95% CI) | 0.62 (0.49-0.79)
p-value | p<0.0001
a Hazard ratios are adjusted for multiplicity but not for stratification variables.
b Based on investigator's assessment.

Figure 8: Kaplan-Meier Curves for Overall Survival in PARAMOUNT

Treatment of Recurrent Disease After Prior Chemotherapy

The efficacy of ALIMTA was evaluated in Study JMEI (NCT00004881), a multicenter, randomized (1:1), open-label study conducted in patients with Stage III or IV NSCLC that had recurred or progressed following one prior chemotherapy regimen for advanced disease. Patients were randomized to receive ALIMTA 500 mg/m^2 intravenously or docetaxel 75 mg/m^2 as a 1-hour intravenous infusion once every 21 days. Patients randomized to ALIMTA also received folic acid and vitamin B12. The study was designed to show that overall survival with ALIMTA was non-inferior to docetaxel, as the major efficacy outcome measure, and that overall survival was superior for patients randomized to ALIMTA compared to docetaxel, as a secondary outcome measure.

A total of 571 patients were enrolled with 283 patients randomized to ALIMTA and 288 patients randomized to docetaxel. The median age was 58 years (range 22 to 87 years); 72% were male; 71% were White, 24% were Asian, 2.8% were Black or African American, 1.8% were Hispanic or Latino, and <2% were other ethnicities; 88% had an ECOG PS of 0 or 1. With regard to tumor characteristics, 75% had Stage IV disease; 53% had adenocarcinoma, 30% had squamous histology; 8% large cell; and 9% had other histologic subtypes of NSCLC.

The efficacy results in the overall population and in subgroup analyses based on histologic subtype are provided in Tables 16 and 17, respectively. Study JMEI did not show an improvement in overall survival in the intent-to-treat population. In subgroup analyses, there was no evidence of a treatment effect on survival in patients with squamous NSCLC; the absence of a treatment effect in patients with NSCLC of squamous histology was also observed Studies JMDB and JMEN [see Clinical Studies (14.1)].

Table 16: Efficacy Results in Study JMEI
Efficacy Parameter | ALIMTA (N=283) | Docetaxel (N=288)
Overall survival
Median (months) (95% CI) | 8.3 (7.0-9.4) | 7.9 (6.3-9.2)
Hazard ratioa (95% CI) | 0.99 (0.82-1.20)
Progression-free survival
Median (months) (95% CI) | 2.9 (2.4-3.1) | 2.9 (2.7-3.4)
Hazard ratioa (95% CI) | 0.97 (0.82-1.16)
Overall response rate (95% CI) | 8.5% (5.2-11.7) | 8.3% (5.1-11.5)
a Hazard ratios are not adjusted for multiplicity or for stratification variables.

Table 17: Exploratory Efficacy Analyses by Histologic Subgroup in Study JMEI
Histologic Subgroups | ALIMTA (N=283) | Docetaxel (N=288)
Non-squamous NSCLC (N=399)
Median (months) (95% CI) | 9.3 (7.8-9.7) | 8.0 (6.3-9.3)
HRa (95% CI) | 0.89 (0.71-1.13)
Adenocarcinoma (N=301)
Median (months) (95% CI) | 9.0 (7.6-9.6) | 9.2 (7.5-11.3)
HRa (95% CI) | 1.09 (0.83-1.44)
Large Cell (N=47)
Median (months) (95% CI) | 12.8 (5.8-14.0) | 4.5 (2.3-9.1)
HRa (95% CI) | 0.38 (0.18-0.78)
Otherb (N=51)
Median (months) (95% CI) | 9.4 (6.0-10.1) | 7.9 (4.0-8.9)
HRa (95% CI) | 0.62 (0.32-1.23)
Squamous NSCLC (N=172)
Median (months) (95% CI) | 6.2 (4.9-8.0) | 7.4 (5.6-9.5)
HRa (95% CI) | 1.32 (0.93-1.86)
a Hazard ratio unadjusted for multiple comparisons.
b Primary diagnosis of NSCLC not specified as adenocarcinoma, large cell carcinoma, or squamous cell carcinoma.

14.2 Mesothelioma

The efficacy of ALIMTA was evaluated in Study JMCH (NCT00005636), a multicenter, randomized (1:1), single-blind study conducted in patients with MPM who had received no prior chemotherapy. Patients were randomized (n=456) to receive ALIMTA 500 mg/m^2 intravenously over 10 minutes followed 30 minutes later by cisplatin 75 mg/m^2 intravenously over two hours on Day 1 of each 21-day cycle or to receive cisplatin 75 mg/m^2 intravenously over 2 hours on Day 1 of each 21-day cycle; treatment continued until disease progression or intolerable toxicity. The study was modified after randomization and treatment of 117 patients to require that all patients receive folic acid 350 mcg to 1000 mcg daily beginning 1 to 3 weeks prior to the first dose of ALIMTA and continuing until 1 to 3 weeks after the last dose, vitamin B12 1000 mcg intramuscularly 1 to 3 weeks prior to first dose of ALIMTA and every 9 weeks thereafter, and dexamethasone 4 mg orally, twice daily, for 3 days starting the day prior to each ALIMTA dose. Randomization was stratified by multiple baseline variables including KPS, histologic subtype (epithelial, mixed, sarcomatoid, other), and gender. The major efficacy outcome measure was overall survival and additional efficacy outcome measures were time to disease progression, overall response rate, and response duration.

A total of 448 patients received at least one dose of protocol-specified therapy; 226 patients were randomized to and received at least one dose of ALIMTA plus cisplatin, and 222 patients were randomized to and received cisplatin. Among the 226 patients who received cisplatin with ALIMTA, 74% received full supplementation with folic acid and vitamin B12 during study therapy, 14% were never supplemented, and 12% were partially supplemented. Across the study population, the median age was 61 years (range: 20 to 86 years); 81% were male; 92% were White, 5% were Hispanic or Latino, 3.1% were Asian, and <1% were other ethnicities; and 54% had a baseline KPS score of 90-100% and 46% had a KPS score of 70-80%. With regard to tumor characteristics, 46% had Stage IV disease, 31% Stage III, 15% Stage II, and 7% Stage I disease at baseline; the histologic subtype of mesothelioma was epithelial in 68% of patients, mixed in 16%, sarcomatoid in 10% and other histologic subtypes in 6%. The baseline demographics and tumor characteristics of the subgroup of fully supplemented patients was similar to the overall study population.

The efficacy results from Study JMCH are summarized in Table 18 and Figure 9.

Table 18: Efficacy Results in Study JMCH
Efficacy Parameter | All Randomized and Treated Patients (N=448) |  | Fully Supplemented Patients (N=331)
Efficacy Parameter | ALIMTA/Cisplatin (N=226) | Cisplatin (N=222) | ALIMTA/Cisplatin (N=168) | Cisplatin (N=163)
Median overall survival (months) | 12.1 | 9.3 | 13.3 | 10.0
(95% CI) | (10.0-14.4) | (7.8-10.7) | (11.4-14.9) | (8.4-11.9)
Hazard ratioa | 0.77 |  | 0.75
Log rank p-value | 0.020 |  | NAb
a Hazard ratios are not adjusted for stratification variables.
b Not a pre-specified analysis.

Figure 9: Kaplan-Meier Curves for Overall Survival in Study JMCH

Based upon prospectively defined criteria (modified Southwest Oncology Group methodology) the objective tumor response rate for ALIMTA plus cisplatin was greater than the objective tumor response rate for cisplatin alone. There was also improvement in lung function (forced vital capacity) in the ALIMTA plus cisplatin arm compared to the control arm.

15 REFERENCES

1. “OSHA Hazardous Drugs.” OSHA. [https://www.osha.gov/hazardous-drugs]

16 HOW SUPPLIED/STORAGE AND HANDLING

How Supplied

ALIMTA, pemetrexed for injection, is a white-to-light yellow or green-yellow lyophilized powder supplied in single-dose vials for reconstitution for intravenous infusion.

NDC 0002-7640-01 (VL7640): Carton containing one (1) single-dose vial of 100 mg pemetrexed.

NDC 0002-7623-01 (VL7623): Carton containing one (1) single-dose vial of 500 mg pemetrexed.

Storage and Handling

Store at 25°C (77°F); excursions permitted to 15 °C -30 °C (59 °F - 86 °F) [see USP Controlled Room Temperature].

ALIMTA is a hazardous drug. Follow applicable special handling and disposal procedures.^1

17 PATIENT COUNSELING INFORMATION

Advise the patient to read the FDA-approved patient labeling (Patient Information).

Premedication and Concomitant Medication: Instruct patients to take folic acid as directed and to keep appointments for vitamin B12 injections to reduce the risk of treatment-related toxicity. Instruct patients of the requirement to take corticosteroids to reduce the risks of treatment-related toxicity [see Dosage and Administration (2.4) and Warnings and Precautions (5.1)].

Myelosuppression: Inform patients of the risk of low blood cell counts and instruct them to immediately contact their physician for signs of infection, fever, bleeding, or symptoms of anemia [see Warnings and Precautions (5.1)].

Renal Failure: Inform patients of the risks of renal failure, which may be exacerbated in patients with dehydration arising from severe vomiting or diarrhea. Instruct patients to immediately contact their healthcare provider for a decrease in urine output [see Warnings and Precautions (5.2)].

Bullous and Exfoliative Skin Disorders: Inform patients of the risks of severe and exfoliative skin disorders. Instruct patients to immediately contact their healthcare provider for development of bullous lesions or exfoliation in the skin or mucous membranes [see Warnings and Precautions (5.3)].

Interstitial Pneumonitis: Inform patients of the risks of pneumonitis. Instruct patients to immediately contact their healthcare provider for development of dyspnea or persistent cough [see Warnings and Precautions (5.4)].

Radiation Recall: Inform patients who have received prior radiation of the risks of radiation recall. Instruct patients to immediately contact their healthcare provider for development of inflammation or blisters in an area that was previously irradiated [see Warnings and Precautions (5.5)].

Increased Risk of Toxicity with Ibuprofen in Patients with Renal Impairment: Advise patients with mild to moderate renal impairment of the risks associated with concomitant ibuprofen use and instruct them to avoid use of all ibuprofen containing products for 2 days before, the day of, and 2 days following administration of ALIMTA [see Dosage and Administration (2.5), Warnings and Precautions (5.6), and Drug Interactions (7)].

Embryo-Fetal Toxicity: Advise females of reproductive potential and males with female partners of reproductive potential of the potential risk to a fetus [see Warnings and Precautions (5.7) and Use in Specific Populations (8.1)]. Advise females of reproductive potential to use effective contraception during treatment with ALIMTA and for 6 months after the last dose. Advise females to inform their prescriber of a known or suspected pregnancy. Advise males with female partners of reproductive potential to use effective contraception during treatment with ALIMTA and for 3 months after the last dose [see Warnings and Precautions (5.7) and Use in Specific Populations (8.3)].

Lactation: Advise women not to breastfeed during treatment with ALIMTA and for 1 week after the last dose [see Use in Specific Populations (8.2)].

Marketed by: Lilly USA, LLC
Indianapolis, IN 46285, USA
Copyright © 2004, 2022, Eli Lilly and Company. All rights reserved.

ALM-0005-USPI-20220831

PATIENT INFORMATION
ALIMTA® (uh-LIM-tuh)
(pemetrexed for injection)
for Intravenous Use

What is ALIMTA?
ALIMTA is a prescription medicine used to treat:

- a kind of lung cancer called non-squamous non-small cell lung cancer (NSCLC). ALIMTA is used:
  - as the first treatment in combination with pembrolizumab and platinum chemotherapy when your lung cancer with no abnormal EGFR or ALK gene has spread (advanced NSCLC).
  - as the first treatment in combination with cisplatin when your lung cancer has spread (advanced NSCLC).
  - alone as maintenance treatment after you have received 4 cycles of chemotherapy that contains platinum for first treatment of your advanced NSCLC and your cancer has not progressed.
  - alone when your lung cancer has returned or spread after prior chemotherapy.
  ALIMTA is not for use for the treatment of people with squamous cell non-small cell lung cancer.
- a kind of cancer called malignant pleural mesothelioma. This cancer affects the lining of the lungs and chest wall. ALIMTA is used in combination with cisplatin as the first treatment for malignant pleural mesothelioma that cannot be removed by surgery or you are not able to have surgery.

ALIMTA has not been shown to be safe and effective in children.

Do not take ALIMTA if you have had a severe allergic reaction to any medicine that contains pemetrexed.

Before taking ALIMTA, tell your healthcare provider about all of your medical conditions, including if you:

- have kidney problems.
- have had radiation therapy.
- are pregnant or plan to become pregnant. ALIMTA can harm your unborn baby.
  Females who are able to become pregnant:
  Your healthcare provider will check to see if you are pregnant before you start treatment with ALIMTA.
  You should use effective birth control (contraception) during treatment with ALIMTA and for 6 months after the last dose. Tell your healthcare provider right away if you become pregnant or think you are pregnant during treatment with ALIMTA.
  Males with female partners who are able to become pregnant should use effective birth control (contraception) during treatment with ALIMTA and for 3 months after the last dose.
- are breastfeeding or plan to breastfeed. It is not known if ALIMTA passes into breast milk. Do not breastfeed during treatment with ALIMTA and for 1 week after the last dose.

Tell your healthcare provider about all the medicines you take, including prescription and over-the-counter medicines, vitamins, and herbal supplements.
Tell your healthcare provider if you have kidney problems and take a medicine that contains ibuprofen. You should avoid taking ibuprofen for 2 days before, the day of, and 2 days after receiving treatment with ALIMTA.

How is ALIMTA given?

- It is very important to take folic acid and vitamin B12 during your treatment with ALIMTA to lower your risk of harmful side effects.
  - Take folic acid exactly as prescribed by your healthcare provider 1 time a day, beginning 7 days (1 week) before your first dose of ALIMTA and continue taking folic acid until 21 days (3 weeks) after your last dose of ALIMTA.
  - Your healthcare provider will give you vitamin B12 injections during treatment with ALIMTA. You will get your first vitamin B12 injection 7 days (1 week) before your first dose of ALIMTA, and then every 3 cycles.
- Your healthcare provider will prescribe a medicine called corticosteroid for you to take 2 times a day for 3 days, beginning the day before each treatment with ALIMTA.
- ALIMTA is given to you by intravenous (IV) infusion into your vein. The infusion is given over 10 minutes.
- ALIMTA is usually given once every 21 days (3 weeks).

What are the possible side effects of ALIMTA?
ALIMTA can cause serious side effects, including:

- Low blood cell counts. Low blood cell counts can be severe, including low white blood cell counts (neutropenia), low platelet counts (thrombocytopenia), and low red blood cell counts (anemia). Your healthcare provider will do blood tests to check your blood cell counts regularly during your treatment with ALIMTA. Tell your healthcare provider right away if you have any signs of infection, fever, bleeding, or severe tiredness during your treatment with ALIMTA.
- Kidney problems, including kidney failure. ALIMTA can cause severe kidney problems that can lead to death. Severe vomiting or diarrhea can lead to loss of fluids (dehydration) which may cause kidney problems to become worse. Tell your healthcare provider right away if you have a decrease in amount of urine.
- Severe skin reactions. Severe skin reactions that may lead to death can happen with ALIMTA. Tell your healthcare provider right away if you develop blisters, skin sores, skin peeling, or painful sores, or ulcers in your mouth, nose, throat or genital area.
- Lung problems (pneumonitis). ALIMTA can cause serious lung problems that can lead to death. Tell your healthcare provider right away if you get any new or worsening symptoms of shortness of breath, cough, or fever.
- Radiation recall. Radiation recall is a skin reaction that can happen in people who have received radiation treatment in the past and are treated with ALIMTA. Tell your healthcare provider if you get swelling, blistering, or a rash that looks like a sunburn in an area that was previously treated with radiation.

The most common side effects of ALIMTA when given alone are:

- tiredness

- nausea

- loss of appetite

The most common side effects of ALIMTA when given with cisplatin are:

- vomiting
- swelling or sores in your mouth or sore throat
- constipation

- low white blood cell counts (neutropenia)
- low platelet counts (thrombocytopenia)
- low red blood cell counts (anemia)

The most common side effects of ALIMTA when given with pembrolizumab and platinum chemotherapy are:

- tiredness and weakness
- constipation
- loss of appetite
- vomiting
- shortness of breath

- nausea
- diarrhea
- rash
- cough
- fever

ALIMTA may cause fertility problems in males. This may affect your ability to father a child. It is not known if these effects are reversible. Talk to your healthcare provider if this is a concern for you.
Your healthcare provider will do blood tests to check for side effects during treatment with ALIMTA. Your healthcare provider may change your dose of ALIMTA, delay treatment, or stop treatment if you have certain side effects.
Tell your healthcare provider if you have any side effect that bothers you or that does not go away.
These are not all the side effects of ALIMTA. For more information, ask your healthcare provider or pharmacist.
Call your doctor for medical advice about side effects. You may report side effects to FDA at 1-800-FDA-1088.

General information about the safe and effective use of ALIMTA.
Medicines are sometimes prescribed for purposes other than those listed in a Patient Information leaflet.
You can ask your pharmacist or healthcare provider for information about ALIMTA that is written for health professionals.

What are the ingredients in ALIMTA?
Active ingredient: pemetrexed
Inactive ingredients: mannitol, hydrochloric acid and/or sodium hydroxide may have been added to adjust pH.
Marketed by: Lilly USA, LLC, Indianapolis, IN 46285, USA
Copyright © 2004, 2022, Eli Lilly and Company. All rights reserved.
ALM-0005-PPI-20220831
For more information, go to www. ALIMTA.com or call 1-800-LILLY-RX (1-800-545-5979).

This Patient Information has been approved by the U.S. Food and Drug Administration.

Revised: August 2022

PACKAGE CARTON – ALIMTA 100 mg single-dose vial

NDC 0002-7640-01

Single-Dose Vial

VL7640

ALIMTA®

pemetrexed for injection

100 mg

For intravenous use only.

Rx only

www.ALIMTA.com

Lilly

PACKAGE CARTON – ALIMTA 500 mg single-dose vial

Single-Dose Vial

NDC 0002-7623-01

VL7623

ALIMTA®

pemetrexed for injection

500 mg

For intravenous use only.

Rx only

www.ALIMTA.com

Lilly